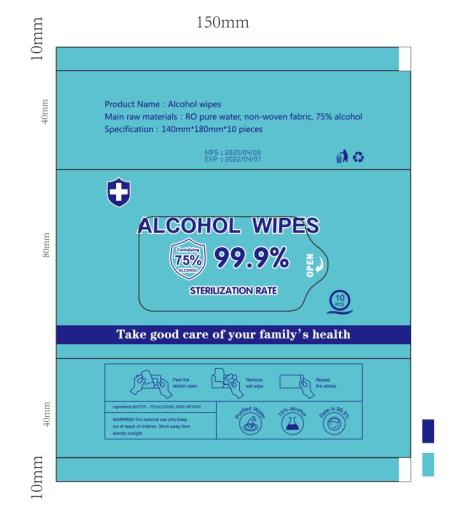 DRUG LABEL: Alcohol wipes
NDC: 54013-001 | Form: CLOTH
Manufacturer: Wenzhou Hongshun Paper Co. , Ltd.
Category: otc | Type: HUMAN OTC DRUG LABEL
Date: 20200608

ACTIVE INGREDIENTS: ALCOHOL 15 mL/10 1
INACTIVE INGREDIENTS: WATER

DOSAGE AND ADMINISTRATION

Place in a cool place to avoid flame

INACTIVE INGREDIENT

water

Non-woven

INDICATIONS AND USAGE

Wipe back and forth with a tissue in skin surface and object surface.

ACTIVE INGREDIENT

alcohol

keep out of reach of children

PURPOSE

Disinfection
Sterilization
No Rinseing

WARNINGS

For external use only; Avid contct with eyes; Keep away from babies and children when not in use.Do not use; In children less than 6 months of age On open skin wounds.When using this product Keep out of eyes. In case of contact with eyes, rinse eyes thoroughly with water.Stop use and ask a doctor if itation or rash ocurs. These may be signs of a serious conditin Keep out of reach of children. If sallowed, get medial help or contacta Poison Control Center right away.